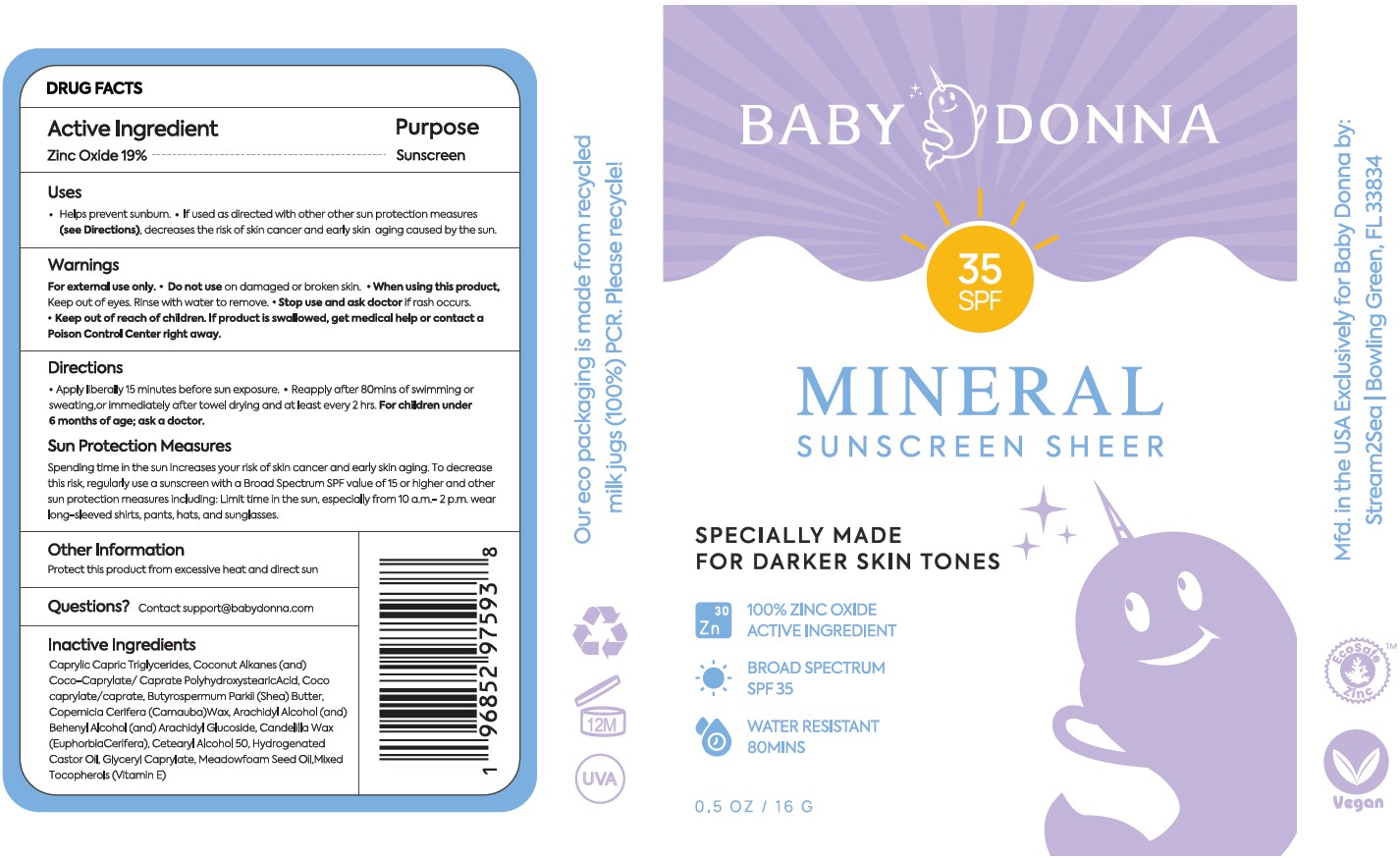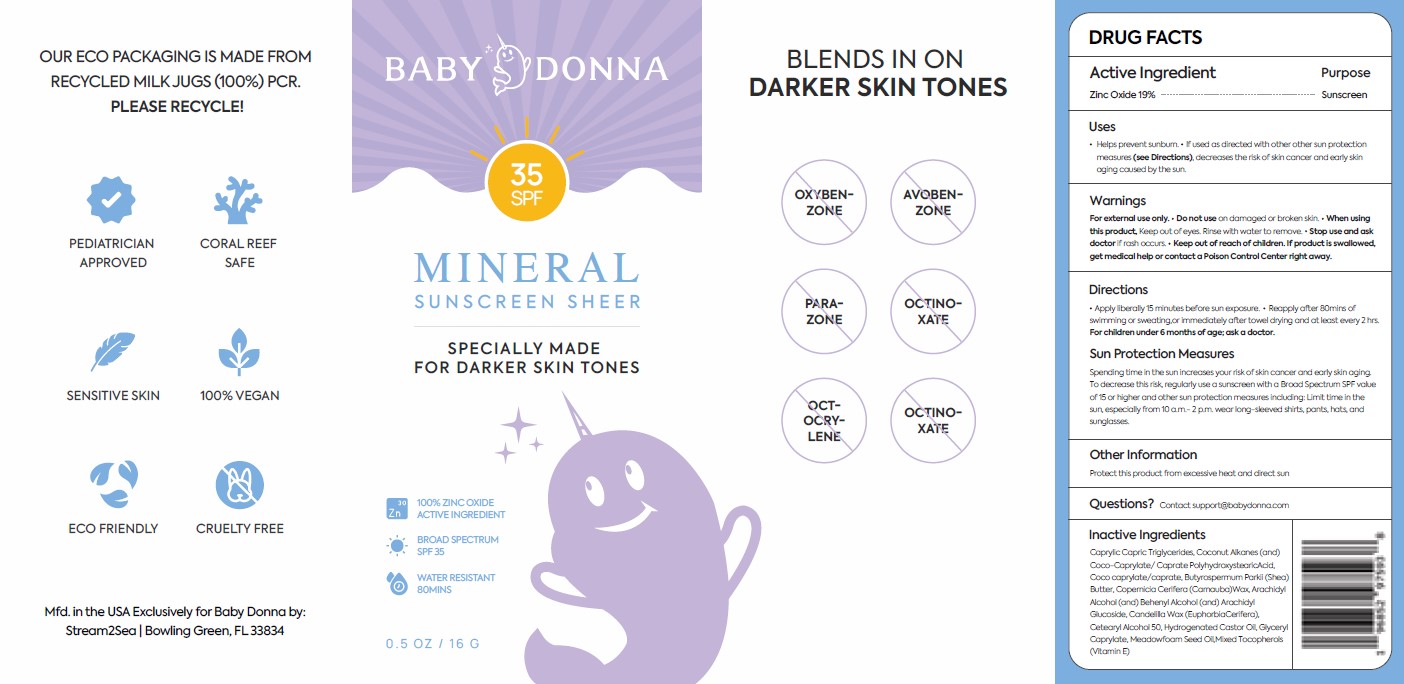 DRUG LABEL: Baby Donna SHeer SPF Sunscreen Stick
NDC: 69555-044 | Form: STICK
Manufacturer: Stream2Sea, LLC
Category: otc | Type: HUMAN OTC DRUG LABEL
Date: 20250112

ACTIVE INGREDIENTS: ZINC OXIDE 19 g/100 g
INACTIVE INGREDIENTS: MEDIUM-CHAIN TRIGLYCERIDES; COCONUT ALKANES; POLYHYDROXYSTEARIC ACID STEARATE; COCOYL CAPRYLOCAPRATE; CARNAUBA WAX; ARACHIDYL ALCOHOL; DOCOSANOL; ARACHIDYL GLUCOSIDE; CANDELILLA WAX; MEADOWFOAM SEED OIL; TOCOPHEROL; CETOSTEARYL ALCOHOL; HYDROGENATED CASTOR OIL; GLYCERYL MONOCAPRYLATE; SHEA BUTTER

Drug Facts

Active Ingredient

Zinc Oxide 19%

Purpose

Sunscreen

Uses

- Helps prevent sunburn.
- If used as directed with other other sun protection measures (see Directions) , decreases the risk of skin cancer and early skin aging caused by the sun.

Warnings

For external use only.

- Do not use on damaged or broken skin.

- When using this product, Keep out of eyes. Rinse with water to remove.

- Stop use and ask doctor if rash occurs

- Keep out of reach of child. If product is swallowed, get medical help or contact a Poison Control Center right away.

Directions

- Apply liberally 15min before sun exposure. Reapply after 80mins of swimming or sweating immediately after towel drying and at least every 2 hrs. For children under 6 months of age; ask a doctor.

Sun Protection Measures

Spending time in the sun increases your risk of skin cancer and early skin aging. To decrease this risk, regularly use a sunscreen with a Broad Spectrum SPF value of 15 or higher and other sun protection measures including: limit time in the sun, especially from 10 a.m.-2 p.m. wear long-sleeved shirts, pants, hats, and sunglasses.

Other Information

Protect this product from excessive heat and direct sun

Questions?

Contact support@babydonna.com

Inactive Ingredients

Caprylic Capric Triglycerides, Coconut Alkanes (and) Coco-Caprylate/Caprate PolyhydroxystearicAcid, Coco caprylate/caprate, Butyrospermum Parkii (Shea) Butter Copernicia Cerifera (Carnauba) Wax, Arachidyl Alcohol (and) Behenyl Alcohol (and) Arachidyl Glucoside Candelilla Wax (Euphorbia Cerifera), Cetearyl Alcohol 50, Hydrogenated Castor Oil, Glyceryl Caprylate Meadowfoam Seed Oil,Mixed Tocopherols (Vitamin E)

Product label

Baby Donna Mineral Sunscreen Sheer 35 SPF- NDC 69555-044-01 -0.5 oz/16 G Stick Label